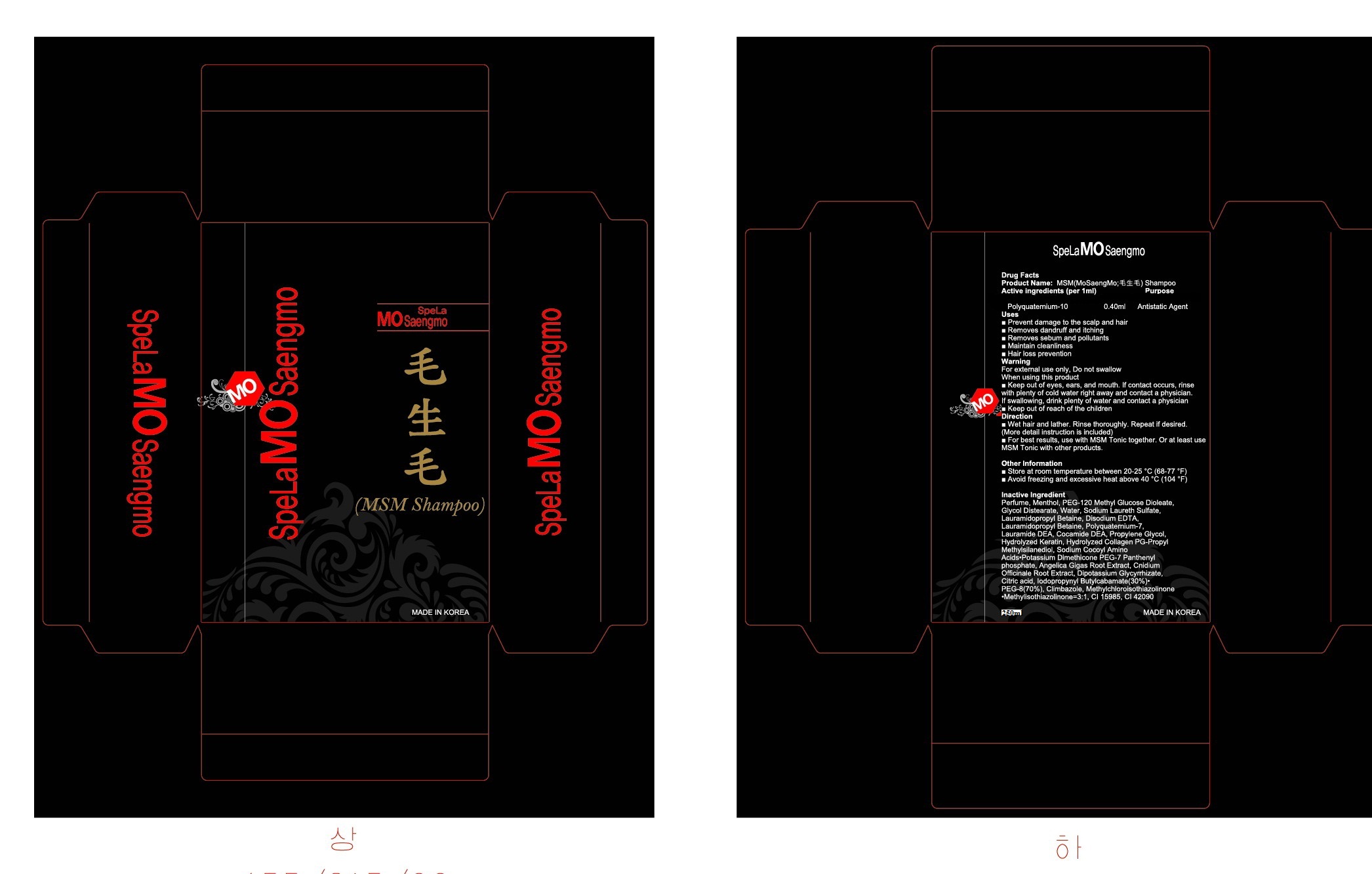 DRUG LABEL: MSM (MoSaengMo)
NDC: 76369-4001 | Form: SHAMPOO
Manufacturer: Handock Cosmetics Inc
Category: otc | Type: HUMAN OTC DRUG LABEL
Date: 20111031

ACTIVE INGREDIENTS: POLYQUATERNIUM-10 (400 CPS AT 2%) 0.4 mL/200 mL
INACTIVE INGREDIENTS: MENTHOL; PEG-120 METHYL GLUCOSE DIOLEATE; GLYCOL DISTEARATE; WATER; SODIUM LAURETH SULFATE; LAURAMIDOPROPYL BETAINE; EDETATE DISODIUM; POLYQUATERNIUM-7 (70/30 ACRYLAMIDE/DADMAC; 1600 KD); LAURIC DIETHANOLAMIDE; COCO DIETHANOLAMIDE; PROPYLENE GLYCOL; COLLAGENASE; DIMETHINDENE; ANGELICA GIGAS ROOT; CNIDIUM OFFICINALE ROOT; GLYCYRRHIZINATE DIPOTASSIUM; CITRIC ACID MONOHYDRATE; IODOPROPYNYL BUTYLCARBAMATE; POLYETHYLENE GLYCOL 400; CLIMBAZOLE; METHYLISOTHIAZOLINONE; FD&C YELLOW NO. 6; FD&C BLUE NO. 1

Drug Facts

active ingredient: polyquatermium-10

inactive ingredient: Perfume, Menthol, PEG-120 Methyl Glucose Dioleate, Glycol Distearate, Water, Sodium Laureth Sulfate, Lauramidopropyl Betaine, Disodium EDTA, Lauramidopropyl Betaine, Polyquaternium-7, Lauramide DEA, Cocamide DEA, Propylene Glycol, Hydrolyzed Keratin, Hydrolyzed Collagen PG-Propyl Methylsilanediol, Sodium Cocoyl Amino Acids·Potassium Dimethicone PEG-7 Panthenyl phosphate, Angelica Gigas Root Extract, Cnidium Officinale Root Extract, Dipotassium Glycyrrhizate, Citric acid, Iodopropynyl Butylcabamate(30%)·PEG-8(70%), Climbazole, Methylchloroisothiazolinone·Methylisothiazolinone, CI 15985, CI 42090

PURPOSE

■ Prevent damage to the scalp and hair
■ Removes dandruff and itching
■ Removes sebum and pollutants
■ Maintain cleanliness
■ Hair loss prevention

keep out of reach of the children

INDICATIONS AND USAGE

■ Wet hair and lather. Rinse thoroughly. Repeat if desired. (More detail instruction is included)

WARNINGS

For external use only, Do not swallow
When using this product
■ Keep out of eyes, ears, and mouth. If contact occurs, rinse with plenty of cold water right away and contact a physician. If swallowing, drink plenty of water and contact a physician

DOSAGE AND ADMINISTRATION

■ For best results, use with MSM Tonic together. Or at least use MSM Tonic with other products